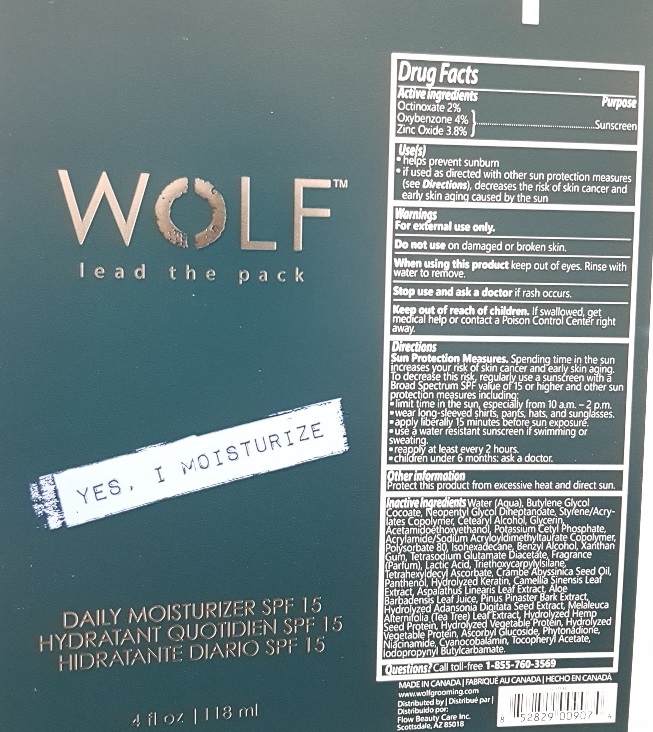 DRUG LABEL: Wolf Daily Moisturizier SPF 15
NDC: 63148-008 | Form: LOTION
Manufacturer: Apollo Health and Beauty Care Inc.
Category: otc | Type: HUMAN OTC DRUG LABEL
Date: 20180601

ACTIVE INGREDIENTS: OCTINOXATE 20 mg/1 mL; OXYBENZONE 40 mg/1 mL; ZINC OXIDE 38 mg/1 mL
INACTIVE INGREDIENTS: WATER; NEOPENTYL GLYCOL DIHEPTANOATE; STYRENE/ACRYLAMIDE COPOLYMER (500000 MW); CETOSTEARYL ALCOHOL; GLYCERIN; POTASSIUM CETYL PHOSPHATE; SODIUM ACRYLOYLDIMETHYLTAURATE-ACRYLAMIDE COPOLYMER (1:1; 90000-150000 MPA.S); POLYSORBATE 80; ISOHEXADECANE; BENZYL ALCOHOL; XANTHAN GUM; TETRASODIUM GLUTAMATE DIACETATE; LACTIC ACID; TETRAHEXYLDECYL ASCORBATE; CRAMBE HISPANICA SUBSP. ABYSSINICA SEED OIL; IODOPROPYNYL BUTYLCARBAMATE; PANTHENOL; GREEN TEA LEAF; ASPALATHUS LINEARIS LEAF; ALOE VERA LEAF; MARITIME PINE; ADANSONIA DIGITATA SEED; TEA TREE OIL; CANNABIS SATIVA SEED; ASCORBYL GLUCOSIDE; PHYTONADIONE; NIACINAMIDE; CYANOCOBALAMIN; .ALPHA.-TOCOPHEROL ACETATE, DL-; TRIETHOXYCAPRYLYLSILANE

Drug Facts

Active ingredients

Octinoxate 2%, Oxybenzone 4%, Zince Oxide 3.8%

Purpose

Sunscreen

Use(s)

- helps prevent sunburn.
- if used as directed with other sun protection measures (see Directions), decreases the risk of skin cancer and early skin aging caused by the sun.

Warnings

For external use only.

Do not use

on damaged or broken skin.

When using this product

keep out of eyes. Rinse with water to remove.

Stop use and ask a doctor

if rash occurs.

Keep out of reach of children

If swallowed, get medical help or contact a Poison Control Center right away.

Directions

Sun Protection Measures. Spending time in the sun increases your risk of skin cancer and early skin aging. To decrease this risk, regularly use a sunscreen with Broad Spectrum SPF value of 15 or higher and other sun protection measure including:

- limit time in the sun, especially from 10 a.m. - 2 p.m.
- wear long-sleeved shirts, pants, hats, and sunglasses.
- use a water resistant sunscreen if swimming or sweating.
- reapply at least every 2 hours.
- children under 6 months: ask doctor

Other information

Protect this product from excessive heat and direct sun.

Inactive ingredients

Water (Aqua), Butylene Glycol Cocoate, Neopentyl Glycol Diheptanoate, Styrene/Acrylates Copolymer, Cetearyl Alcohol, Glycerin, Acetamidoethoxyethanol, Potassium Cetyl Phosphate, Acrylamide/Sodium Acryloyldimethyltaurate Copolymer, Polysorbate 80, Isohexadecane, Benzyl Alcohol, Xanthan Gum, Tetrasodium Glutamate Diacetate, Fragrance (Parfum), Lactic Acid, Triethoxycaprylylsilane, Tetrahexydecyl Ascorbate, Crambe Abyssinica Seed Oil, Panthenol, Hydrolyzed Keratin, Camellia Sinensis Leaf Extract, Aspalathus Linearis Leaf Extract, Aloe Barbadensis Leaf Juice, Pinus Pinaster Bark Extract, Hydrolyzed Adansonia Digitata Seed Extract, Melaleuca Alternifolia (Tea Tree) Leaf Extract, Hydrolyzed Hemp Protein, Hydrolyzed Vegetable Protein, Ascorbyl Glucoside, Phytonadione, Niacinamide, Cyanocobalamin, Tocopheryl Acetate, Iodopropynyl Butylcarbamate.

Questions?

Call toll-free 1-855-760-3569